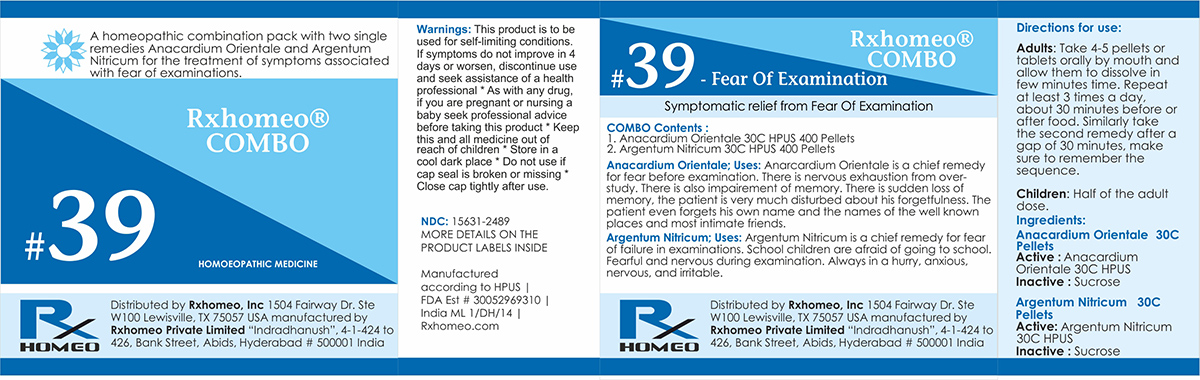 DRUG LABEL: Rxhomeo Homeopathic Combo-39
NDC: 15631-2489 | Form: KIT | Route: ORAL
Manufacturer: Rxhomeo Private Limited d.b.a.
Category: homeopathic | Type: HUMAN OTC DRUG LABEL
Date: 20161014

ACTIVE INGREDIENTS: SEMECARPUS ANACARDIUM JUICE 3 [hp_X]/1 1; SILVER NITRATE 6 [hp_X]/1 1
INACTIVE INGREDIENTS: SUCROSE; SUCROSE

ACTIVE INGREDIENT

ANACARDIUM ORIENTALE HPUS 3X and higher

ARGENTUM NITRICUM HPUS 6X and higher

USES

A homeopathic combination pack with two single remedies Anacardium Orientale and Argentum Nitricum for the treatment of symptoms associated with fear of examinations.

Anacardium Orientale;Uses: Anarcardium Orientale is a chief remedy for fear before examination. There is nervous exhaustion from over-study. There is also impairement of memory. There is sudden loss of memory, the patient is very much disturbed about his forgetfulness. The patient even forgets his own name and the names of the well known places and most intimate friends.

Argentum Nitricum;Uses: Argentum Nitricum is a chief remedy for fear of failure in examinations. School children are afraid of going to school. Fearful and nervous during examination. Always in a hurry, anxious, nervous, and irritable.

INDICATIONS

Condition listed above or as directed by the physician

DOSAGE

PELLETS included in the Combo

Adults- Take 4 or 6 Pellets by mouth, three times daily or as suggested by physician. Children 2 years and older- take 1/2 the adult dose.

WARNINGS

This product is to be used for self-limiting conditions

STOP USE

If symptoms do not improve in 4 days, or worsen, discontinue use and seek assistance of health professional

KEEP OUT OF REACH OF CHILDREN

Keep this and all medication out of reach of children

Do not use if capseal is broken or missing.

Close the cap tightly after use.

INACTIVE INGREDIENTS

Sucrose for Pellets.

STORAGE

Store in a cool dark place

QUESTIONS OR COMMENTS

www.Rxhomeo.com | 1.888.2796642 | info@rxhomeo.com
Rxhomeo, Inc 1504 Fairway Dr. Ste W 100 Lewisville, TX 75057 USA